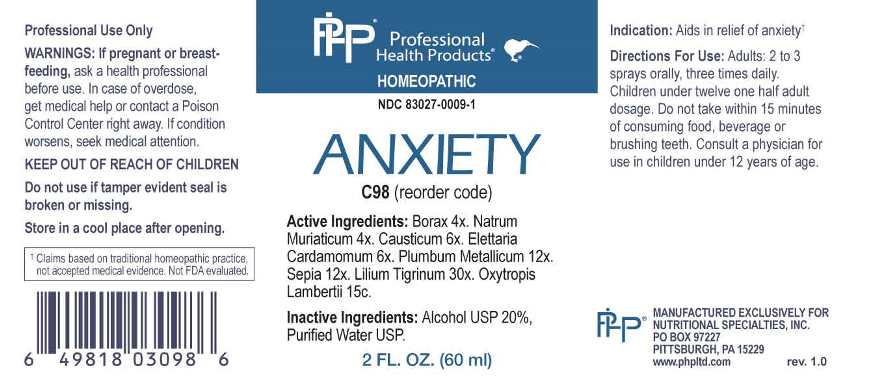 DRUG LABEL: Anxiety
NDC: 83027-0009 | Form: SPRAY
Manufacturer: Nutritional Specialties, Inc.
Category: homeopathic | Type: HUMAN OTC DRUG LABEL
Date: 20230403

ACTIVE INGREDIENTS: SODIUM BORATE 4 [hp_X]/1 mL; SODIUM CHLORIDE 4 [hp_X]/1 mL; CAUSTICUM 6 [hp_X]/1 mL; CARDAMOM 6 [hp_X]/1 mL; LEAD 12 [hp_X]/1 mL; SEPIA OFFICINALIS JUICE 12 [hp_X]/1 mL; LILIUM LANCIFOLIUM WHOLE FLOWERING 30 [hp_X]/1 mL; OXYTROPIS LAMBERTII TOP 16 [hp_C]/1 mL
INACTIVE INGREDIENTS: WATER; ALCOHOL

DRUG FACTS:

ACTIVE INGREDIENTS:

Borax 4X, Natrum Muriaticum 4X, Causticum 6X, Elettaria Cardamomum 6X, Plumbum Metallicum 12X, Sepia 12X, Lilium Tigrinum 30X, Oxytropis Lambertii 15C.

PURPOSE:

Aids in relief of anxiety.†

†Claims based on traditional homeopathic practice, not accepted medical evidence. Not FDA evaluated.

WARNINGS:

Professional Use Only

If pregnant or breast-feeding, ask a health professional before use.

In case of overdose, get medical help or contact a Poison Control Center right away.

If condition worsens, seek medical attention.

KEEP OUT OF REACH OF CHILDREN

Do not use if tamper evident seal is broken or missing.

Store in a cool place after opening

KEEP OUT OF REACH OF CHILDREN:

In case of overdose, get medical help or contact a Poison Control Center right away.

DIRECTIONS:

Adults: 2 to 3 sprays orally, three times daily. Children under twelve one half adult dosage. Do not take within 15 minutes of consuming food, beverage or brushing teeth. Consult a physician for use in children under 12 years of age.

INDICATIONS:

Aids in relief of anxiety.†

†Claims based on traditional homeopathic practice, not accepted medical evidence. Not FDA evaluated.

INACTIVE INGREDIENTS:

Alcohol USP 20%, Purified Water USP.

QUESTIONS:

MANUFACTURED EXCLUSIVELY FOR

NUTRITIONAL SPECIALTIES, INC.

PO BOX 97227

PITTSBURG, PA 15229

www.phpltd.com

PACKAGE LABEL DISPLAY:

Professional

Health Products

HOMEOPATHIC

NDC 83027-0009-1

ANXIETY

2 FL. OZ (60 ml)